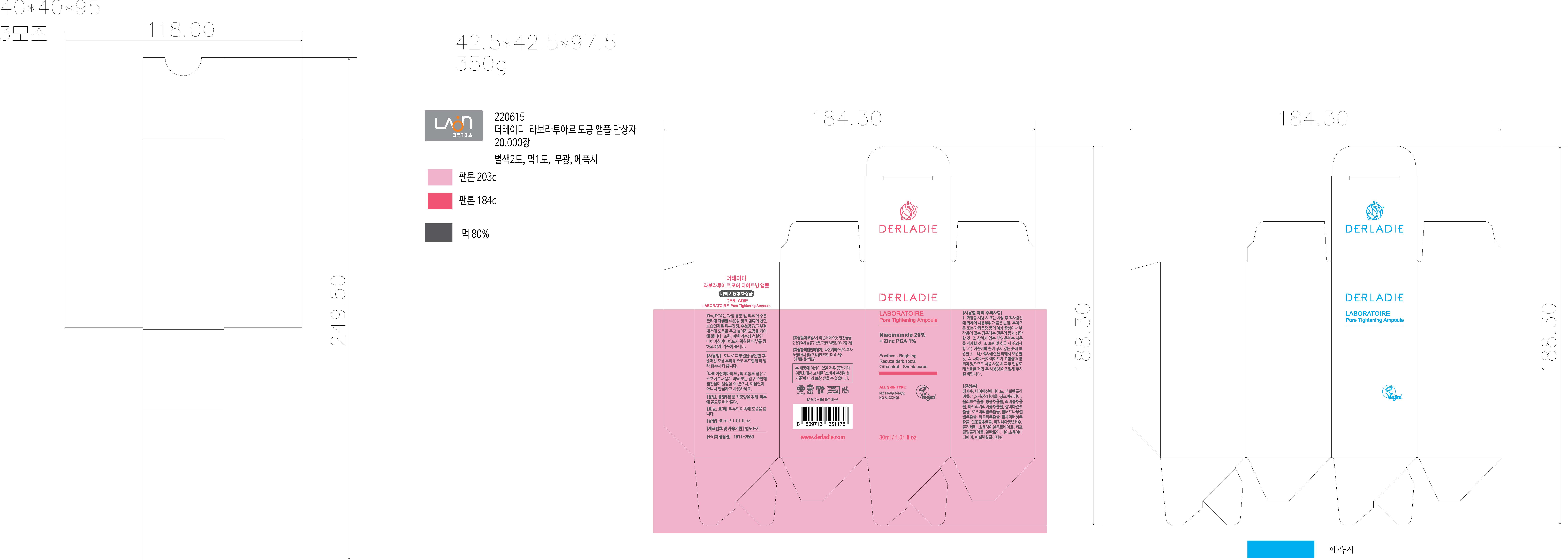 DRUG LABEL: DERLADIE LABORATOIRE PORE TIGHTENING AMPOULE
NDC: 82083-0028 | Form: LIQUID
Manufacturer: LAON COMMERCE co ltd
Category: otc | Type: HUMAN OTC DRUG LABEL
Date: 20231207

ACTIVE INGREDIENTS: NIACINAMIDE 20 g/100 mL
INACTIVE INGREDIENTS: WATER; CENTELLA ASIATICA

ACTIVE INGREDIENT

Niacinamide

INACTIVE INGREDIENT

Water
Butylene Glycol
1,2-Hexanediol
Zinc PCA
Olea Europaea (Olive) Fruit Extract
Centella Asiatica Extract
Portulaca Oleracea Extract
Chamomilla Recutita (Matricaria) Flower Extract
Salvia Officinalis (Sage) Leaf Extract
Rosmarinus Officinalis (Rosemary) Leaf Extract
Salix Alba (Willow) Bark Extract
Melaleuca Alternifolia (Tea Tree) Extract
Tremella Fuciformis (Mushroom) Extract
Nelumbo Nucifera Flower Extract
Hamamelis Virginiana (Witch Hazel) Water
Glycerin
Sodium Hyaluronate
Caprylyl Glycol
Allantoin
Disodium EDTA
Ethylhexylglycerin

PURPOSE

skin protect

KEEP OUT OF REACH OF THE CHILDREN

INDICATIONS AND USAGE

After preparing the skin texture with toner, gently spread it over the enlarged pores and let it absorb.

WARNINGS

1. During using product or after use, if there are any
abnormal symptoms or side effects such as red spots,
swelling or itching in the area of use due to direct
sunlight, consult with a specialist.
2. Refrain from using on areas with scars, etc.
3. Precautions for storage and handling
A) Keep out of reach of chil
dren
B) Store away from direct sunlight
4.
Since a high dose of niacinamide is prescribed, please
adjust the amount after performing a skin sensitivity test
when using for the first time

DOSAGE AND ADMINISTRATION

topical use only